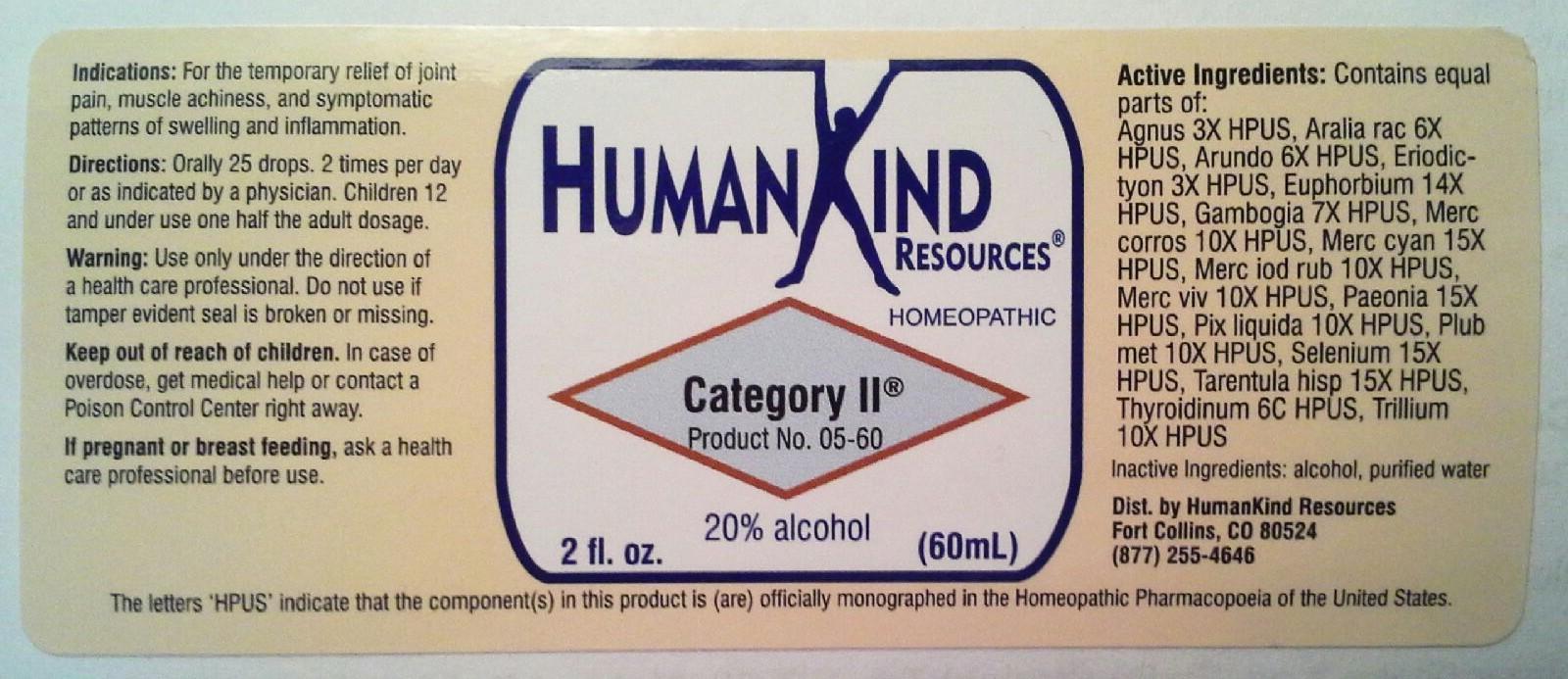 DRUG LABEL: Category II
NDC: 64616-083 | Form: LIQUID
Manufacturer: Vitality Works, Inc
Category: homeopathic | Type: HUMAN OTC DRUG LABEL
Date: 20251217

ACTIVE INGREDIENTS: TRILLIUM ERECTUM ROOT 10 [hp_X]/1 mL; CHASTE TREE 3 [hp_X]/1 mL; ARALIA RACEMOSA ROOT 6 [hp_X]/1 mL; ARUNDO PLINIANA ROOT 6 [hp_X]/1 mL; EUPHORBIA RESINIFERA RESIN 14 [hp_X]/1 mL; ERIODICTYON CALIFORNICUM LEAF 3 [hp_X]/1 mL; GAMBOGE 7 [hp_X]/1 mL; MERCURIC CHLORIDE 10 [hp_X]/1 mL; MERCURIC CYANIDE 15 [hp_X]/1 mL; MERCURIC IODIDE 10 [hp_X]/1 mL; MERCURY 10 [hp_X]/1 mL; PAEONIA OFFICINALIS ROOT 15 [hp_X]/1 mL; PINE TAR 10 [hp_X]/1 mL; LEAD 10 [hp_X]/1 mL; SELENIUM 15 [hp_X]/1 mL; LYCOSA TARANTULA 15 [hp_X]/1 mL; THYROID, UNSPECIFIED 6 [hp_C]/1 mL
INACTIVE INGREDIENTS: ALCOHOL; WATER

Category II

Category II

Agnus Castus 3X Mercurius Cyanatus 15X Tarentula Hispana 15X
Aralia Racemosa 6X Mercurius Iodatus Ruber 10X Thyrodiunum 4C
Arundo Mauritanica 6X Mercurius Vivus 10X Trillum Pendulum 10X
Eriodictyon Californicum 3X Paeonia Officinalis 15X
Euphorbium Officinarum 14X Pix Liquida 10X
Gambogia 7X Plumbum Metallicum 10X
Mercurius Corrosivus 10X Selenium Metallicum 15X

Category II

Alcohol, Purified Water

Category II

Use under the direction of a health care professional. Do not use if tamper evident seal is broken or missing.

Category II

Keep out of reach of children. In case of overdose, get medical help or contact a Poison Control Center reght away.

Category II

For the temporary relief of joint pain, muscle achiness, and symptomatic patterns of swelling and inflammation.

Category II

Orally 25 drops, 2 times per day or as indicated by a physician. Children 12 and under use one half the adult dosage.

Category II

Temporarly eases runny nose, sore throat, sinus swelling, aching joints.